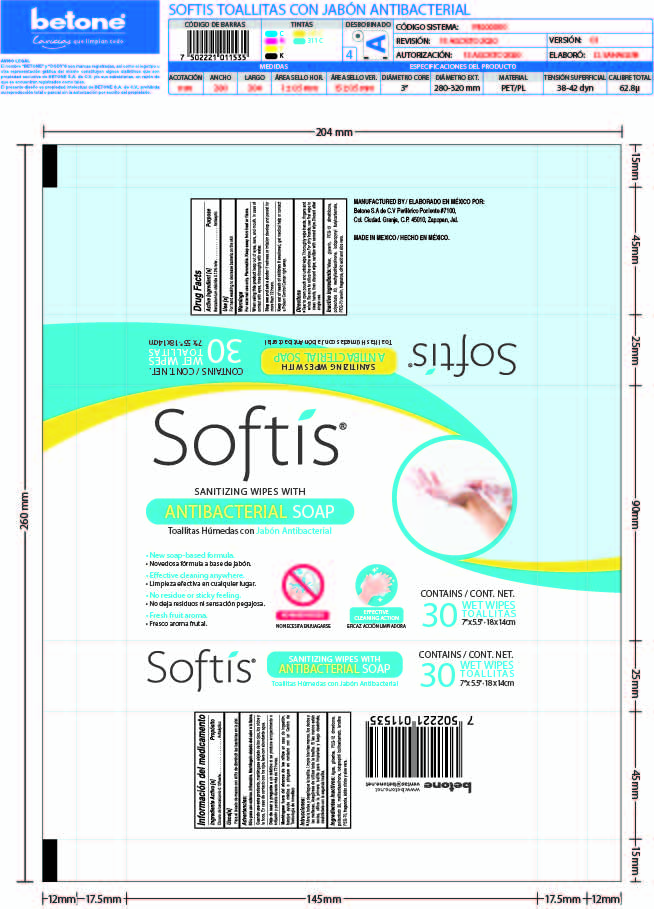 DRUG LABEL: SOFTIS
NDC: 77824-004 | Form: CLOTH
Manufacturer: Betone, S.A de C.V.
Category: otc | Type: HUMAN OTC DRUG LABEL
Date: 20200909

ACTIVE INGREDIENTS: BENZALKONIUM CHLORIDE 0.12 g/100 mL; POLYAMINOPROPYL BIGUANIDE 0.5 g/100 mL
INACTIVE INGREDIENTS: DIMETHICONE PEG-7 PANTHENYL PHOSPHATE (12 PANTHENOL) 0.12 mL/100 mL; ABRONIA FRAGRANS FLOWER 0.1 mL/100 mL; IODOPROPYNYL BUTYLCARBAMATE 0.17 mL/100 mL; DECYL GLUCOSIDE 0.2 mL/100 mL; ALOE VERA FLOWER 0.08 mL/100 mL; CITRIC ACID MONOHYDRATE 0.04 mL/100 mL; METHYLISOTHIAZOLINONE 0.17 mL/100 mL; GLYCERIN 1 mL/100 mL; DISODIUM COCOAMPHODIACETATE 0.6 mL/100 mL; WATER; POLYSORBATE 20 0.2 mL/100 mL

BETONE- Toallitas Jabón

Active Ingredient(s)

Belzalkonium chloride 0.12 % w/w. Purpose: Antiseptic

Polyaminopropyl Biguanide 0.5% w/w Purpose: Antiseptic

Purpose

Antiseptic, Hand Sanitizer

Use

Hand Sanitizer to help reduce bacteria that potentially can cause disease. For use when soap and water are not available.

Warnings

For external use only. Flammable. Keep away from heat or flame

Do not use

- in children less than 2 months of age
- on open skin wounds

When using this product keep out of eyes, ears, and mouth. In case of contact with eyes, rinse eyes thoroughly with water.
Stop use and ask a doctor if irritation or rash occurs. These may be signs of a serious condition.
Keep out of reach of children. If swallowed, get medical help or contact a Poison Control Center right away.

Stop use and ask a doctor if irritation or rash occurs. These may be signs of a serious condition.

Keep out of reach of children. If swallowed, get medical help or contact a Poison Control Center right away.

Directions

- Place enough product on hands to cover all surfaces. Rub hands together until dry.
- Supervise children under 6 years of age when using this product to avoid swallowing.

Other information

- Store between 15-30C (59-86F)
- Avoid freezing and excessive heat above 40C (104F)

Inactive ingredients

Water, glycerin, disodium cocoamphodiacetate, polysorbate 20, decyl glucoside, iodopropynyl butyñcarmate, methylisothiazolinone, PEF- 12 dimethicone, fragrance, aleo vera and citric acid.

Package Label - Principal Display Panel

PDP 150 g NDC: 77824-002-02